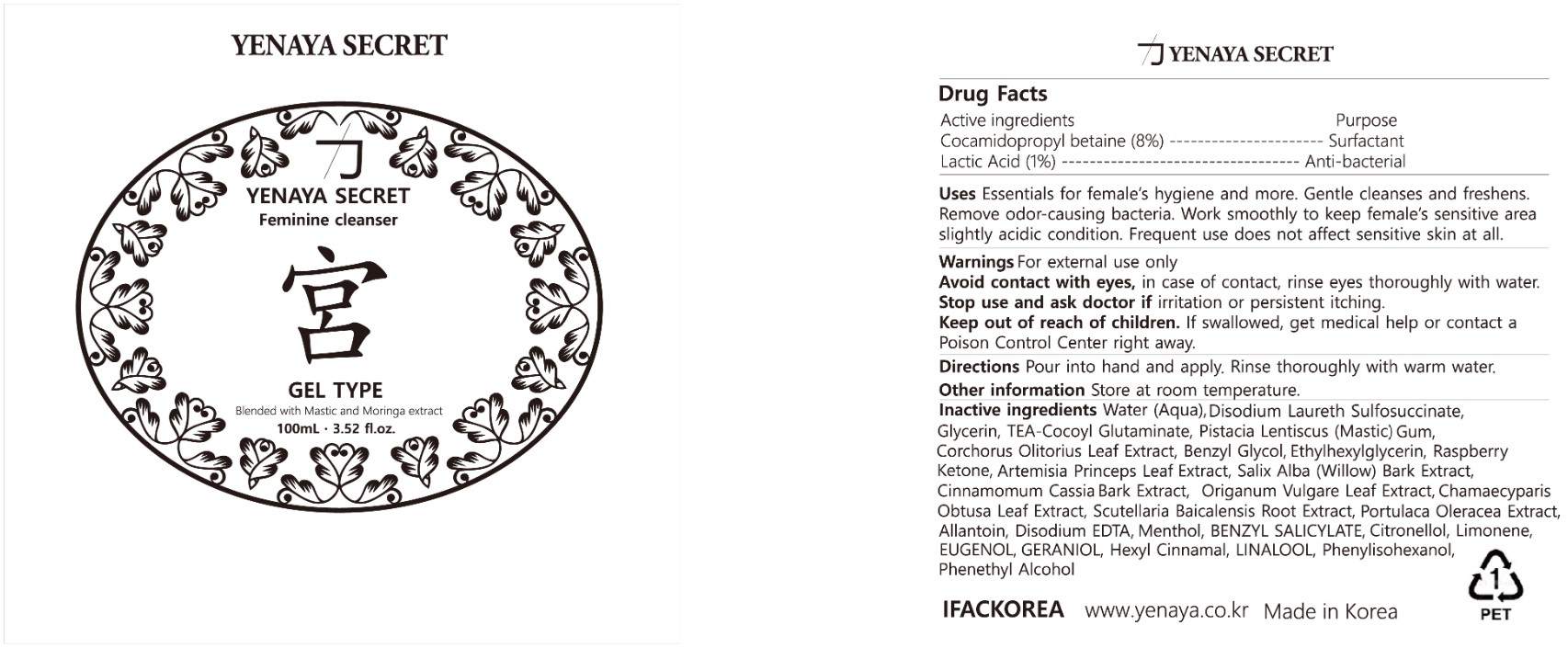 DRUG LABEL: YENAYA SECRET GUNG CLEANSER
NDC: 81873-202 | Form: GEL
Manufacturer: IFACKOREA CO., LTD
Category: otc | Type: HUMAN OTC DRUG LABEL
Date: 20241231

ACTIVE INGREDIENTS: COCAMIDOPROPYL BETAINE 8 mg/100 mL; LACTIC ACID, UNSPECIFIED FORM 1 mg/100 mL
INACTIVE INGREDIENTS: DISODIUM LAURETH SULFOSUCCINATE; SCUTELLARIA BAICALENSIS ROOT; 4-(P-HYDROXYPHENYL)-2-BUTANONE; ARTEMISIA PRINCEPS LEAF; SALIX ALBA BARK; OREGANO; PURSLANE; EDETATE DISODIUM ANHYDROUS; .BETA.-CITRONELLOL, (R)-; BENZYL SALICYLATE; EUGENOL; PHENYLETHYL ALCOHOL; LINALOOL, (+/-)-; CHINESE CINNAMON; PHENYLISOHEXANOL; TRIETHANOLAMINE COCOYL GLUTAMINATE; GERANIOL; CHAMAECYPARIS OBTUSA LEAF; ALLANTOIN; WATER; .ALPHA.-HEXYLCINNAMALDEHYDE; CORCHORUS OLITORIUS LEAF; ETHYLHEXYLGLYCERIN; GLYCERIN; PISTACIA LENTISCUS RESIN OIL; ETHYLENE GLYCOL MONOBENZYL ETHER; MENTHOL, UNSPECIFIED FORM

81873-202 YENAYA SECRET GUNG CLEANSER

Active ingredients

Cocamidopropyl betaine (8%)
Lactic Acid (1%)

Purpose

Surfactant

Anti-bacterial

Uses

Essentials for female’s hygiene and more. Gentle cleanses and freshens. Removes odor causing bacteria. Work smoothly to keep female’s sensitive area slightly acidic condition. Frequent use does not affect sensitive skin at all.

Warnings

For external use only

When using this product

Avoid contact with eyes, in case of contact, rinse eyes thoroughly with water.

Stop use and ask doctor if

irritation or persistent itching.

Keep out of reach of children

If swallowed, get medical help or contact a Poison Control Center right away.

Directions

Pour into hand and apply. Rinse thoroughly with warm water.

Other information

Store at room temperature

Inactive ingredients

Water (Aqua), Dis odium Laureth Sulfate, Glycerin, TEA Cocoyl Glutaminate, Pistacia Lentiscus (Ma stic) Gum, Corchorus Olitorius Leaf Extract, Benzyl Glycol, Ethylhexylglycerin, Raspberry Ketone, Artemisia Princeps Leaf Extract, Salix Alba (Willow) Bark Extract, Cinnamomum Cassia Bark Extract, Origanum Vulgare Leaf Extract, Chamaecyparis Obtusa Leaf Extract, Scutellaria Baicalensis Root Extract, Portulaca Oleracea Extract, Allantoin, Disodium EDTA, Menthol, BENZYL SALICYLATE, Citronellol, Limonene, EUGENOL, GERANIOL, Hexyl Cinnamal, LINALOOL, Phenylisohexanol, Phenelthyl